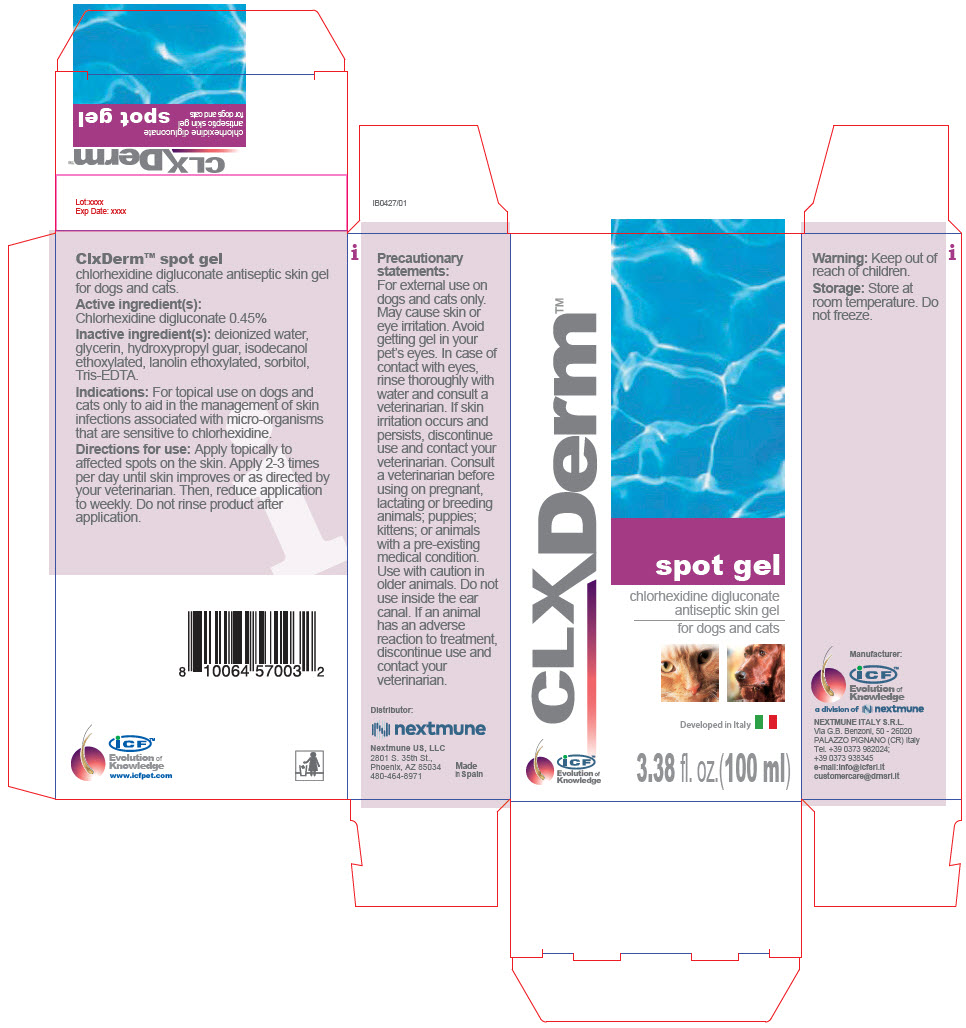 DRUG LABEL: Clx Derm Spot
NDC: 86127-004 | Form: GEL
Manufacturer: Nextmune AB
Category: animal | Type: OTC ANIMAL DRUG LABEL
Date: 20220112

ACTIVE INGREDIENTS: CHLORHEXIDINE GLUCONATE 4.5 mg/1 mL
INACTIVE INGREDIENTS: water; glycerin; GUARAPROLOSE (3500 MPA.S AT 1%); isodecyl alcohol; Sorbitol; PEG-75 Lanolin; TROMETHAMINE; EDETATE SODIUM

ClxDerm™ spot gel

VETERINARY INDICATIONS

chlorhexidine digluconate antiseptic skin gel for dogs and cats.

Active ingredient(s):

Chlorhexidine digluconate 0.45%

Inactive ingredient(s): deionized water, glycerin, hydroxypropyl guar, isodecanol ethoxylated, lanolin ethoxylated, sorbitol, Tris-EDTA.

INDICATIONS AND USAGE

Indications: For topical use on dogs and cats only to aid in the management of skin infections associated with micro-organisms that are sensitive to chlorhexidine.

DOSAGE AND ADMINISTRATION

Directions for use: Apply topically to affected spots on the skin. Apply 2-3 times per day until skin improves or as directed by your veterinarian. Then, reduce application to weekly. Do not rinse product after application.

PRECAUTIONS

Precautionary statements:

For external use on dogs and cats only. May cause skin or eye irritation. Avoid getting gel in your pet's eyes. In case of contact with eyes, rinse thoroughly with water and consult a veterinarian. If skin irritation occurs and persists, discontinue use and contact your veterinarian. Consult a veterinarian before using on pregnant, lactating or breeding animals; puppies; kittens; or animals with a pre-existing medical condition. Use with caution in older animals. Do not use inside the ear canal. If an animal has an adverse reaction to treatment, discontinue use and contact your veterinarian.

Warning: Keep out of reach of children.

Storage: Store at room temperature. Do not freeze.

Manufacturer:

iCF™
Evolution of
Knowledge

a division of

NEXTMUNE ITALY S.R.L.
Via G.B. Benzoni, 50 - 26020
PALAZZO PIGNANO (CR) Italy
Tel. +39 0373 982024;
+39 0373 938345
e-mail:info@icfsrl.it
customercare@drnsrl.it

Distributor:

Nextmune US, LLC
2801 S. 35th St.,
Phoenix, AZ 85034
480-464-8971

Made
in Spain

iCF™
Evolution of
Knowledge

www.icfpet.com

PRINCIPAL DISPLAY PANEL - 100 ml Bottle Carton

CLXDerm™

spot gel

chlorhexidine digluconate
antiseptic skin gel

for dogs and cats

Developed in Italy

iCF™
Evolution of
Knowledge

3.38 fl. oz.(100 ml)